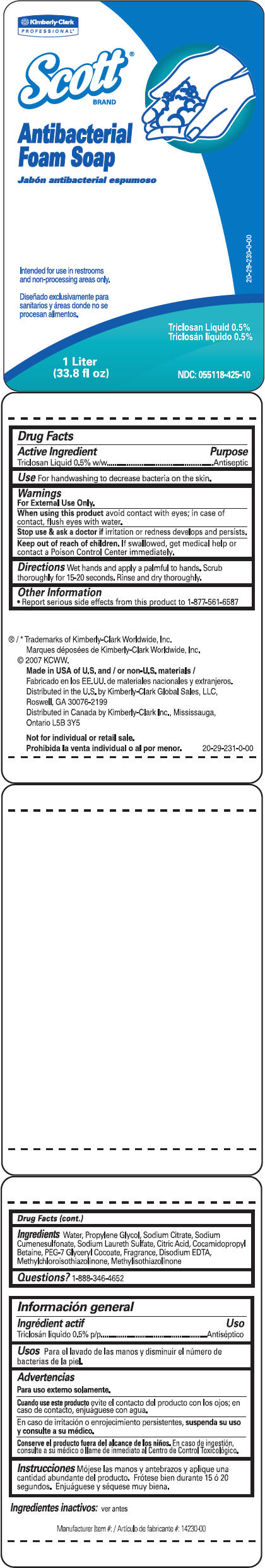 DRUG LABEL: Scott Antibacterial
NDC: 55118-425 | Form: SOLUTION
Manufacturer: Kimberly-Clark Corporation
Category: otc | Type: HUMAN OTC DRUG LABEL
Date: 20141112

ACTIVE INGREDIENTS: Triclosan 5 g/1 L
INACTIVE INGREDIENTS: Water; Propylene Glycol; Sodium Citrate; Sodium Cumenesulfonate; Sodium Laureth-3 Sulfate; Citric Acid Monohydrate; Cocamidopropyl Betaine; Edetate Disodium; Methylchloroisothiazolinone; Methylisothiazolinone

Scott®
BRAND
Antibacterial
Foam Soap

Drug Facts

Active Ingredient

Triclosan Liquid 0.5% w/w

Purpose

Antiseptic

Use

For handwashing to decrease bacteria on the skin.

Warnings

For External Use Only.

When using this product avoid contact with eyes; in case of contact, flush eyes with water.

Stop use & ask a doctor if irritation or redness develops and persists.

Keep out of reach of children. If swallowed, get medical help or contact a Poison Control Center immediately.

Directions

Wet hands and apply a palmful to hands. Scrub thoroughly for 15-20 seconds. Rinse and dry thoroughly.

Other Information

- Report serious side effects from this product to 1-877-561-6587

Ingredients

Water, Propylene Glycol, Sodium Citrate, Sodium Cumenesulfonate, Sodium Laureth Sulfate, Citric Acid, Cocamidopropyl Betaine, PEG-7 Glyceryl Cocoate, Fragrance, Disodium EDTA, Methylchloroisothiazolinone, Methylisothiazolinone

Questions?

1-888-346-4652

Distributed in the U.S. by Kimberly-Clark Global Sales, LLC,
Roswell, GA 30076-2199

PRINCIPAL DISPLAY PANEL - 1 Liter Bottle Label

Kimberly-Clark
PROFESSIONAL*

Scott®
BRAND

Antibacterial
Foam Soap

Intended for use in restrooms
and non-processing areas only.

Triclosan Liquid 0.5%

1 Liter
(33.8 fl oz)

NDC: 055118-425-10